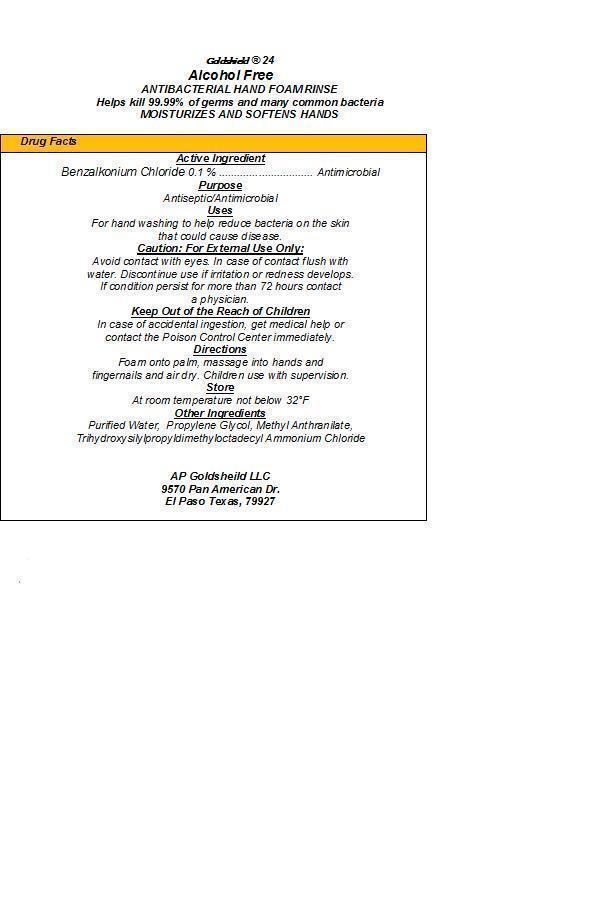 DRUG LABEL: GOLDSHIELD 24
NDC: 40092-500 | Form: SOLUTION
Manufacturer: AP GOLDSHIELD LLC
Category: otc | Type: HUMAN OTC DRUG LABEL
Date: 20230628

ACTIVE INGREDIENTS: BENZALKONIUM CHLORIDE 0.001 g/1 g
INACTIVE INGREDIENTS: WATER; PROPYLENE GLYCOL; DIMETHYLOCTADECYL(3-(TRIMETHOXYSILYL)PROPYL)AMMONIUM CHLORIDE; METHYL ANTHRANILATE

DRUG FACTS

DESCRIPTION

- GOLDSHIELD 24 ALCOHOL FREE ANTIBACTERIAL HAND FOAM RINSE contains 0.1 % benzalkonium chloride antimicrobial agent, formulated with purified water, propylene glycol, methyl anthranilate and trihydroxysilylpropyldimethyloctadecyl ammonium chloride. Helps kill 99.99 % of germs and many common bacteria. Moisturizes and softens hands.

ACTIVE INGREDIENT

- Benzalkonium Chloride 0.1 % ------------------------------------ Antimicrobial

PURPOSE

- Antiseptic/Antimicrobial

INDICATIONS AND USAGE

- For hand washing to help reduce bacteria on the skin that could cause disease.

WARNINGS

- Caution: For External Use Only. Avoid contact with eyes. In case of contact flush with water. Discontinue use if irritation or redness develops. If condition persists for more than 72 hours contact a physician.

KEEP OUT OF REACH OF CHILDREN

- Keep out of the Reach of Children. In case of accidental ingestion, get medical help or contact the Poison Control Center immediately.

DOSAGE AND ADMINISTRATION

- Directions: Foam onto palm, massage into hands and fingernails and air dry. Children use with supervision.

STORAGE AND HANDLING

- Store at room temperature not below 32 degrees F.

INACTIVE INGREDIENT

- Purified Water, Propylene Glycol, Methyl Anthranilate and Trihydroxysilylpropyldimethyloctadecyl Ammonium Chloride

PACKAGE LABEL

LABE